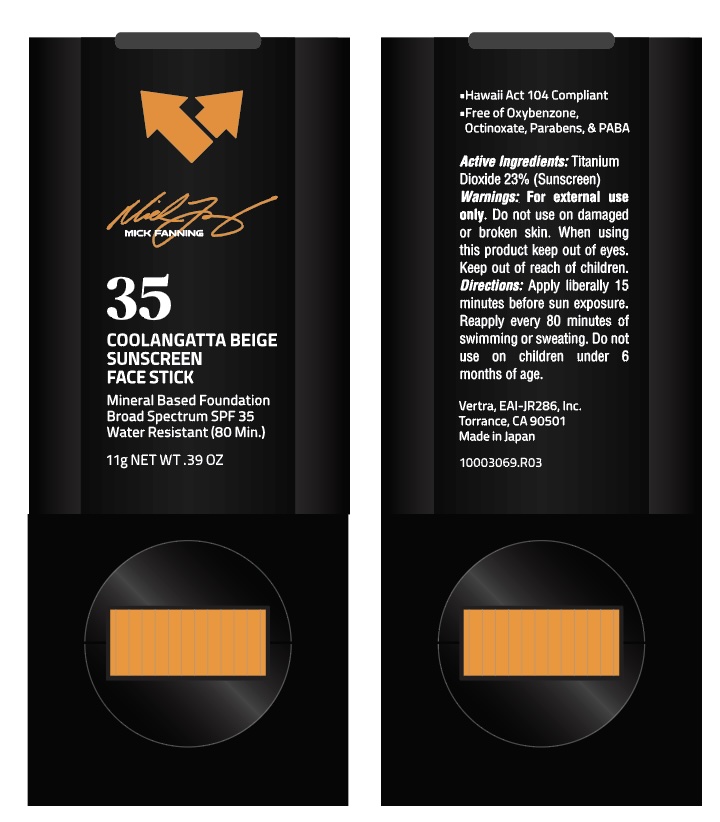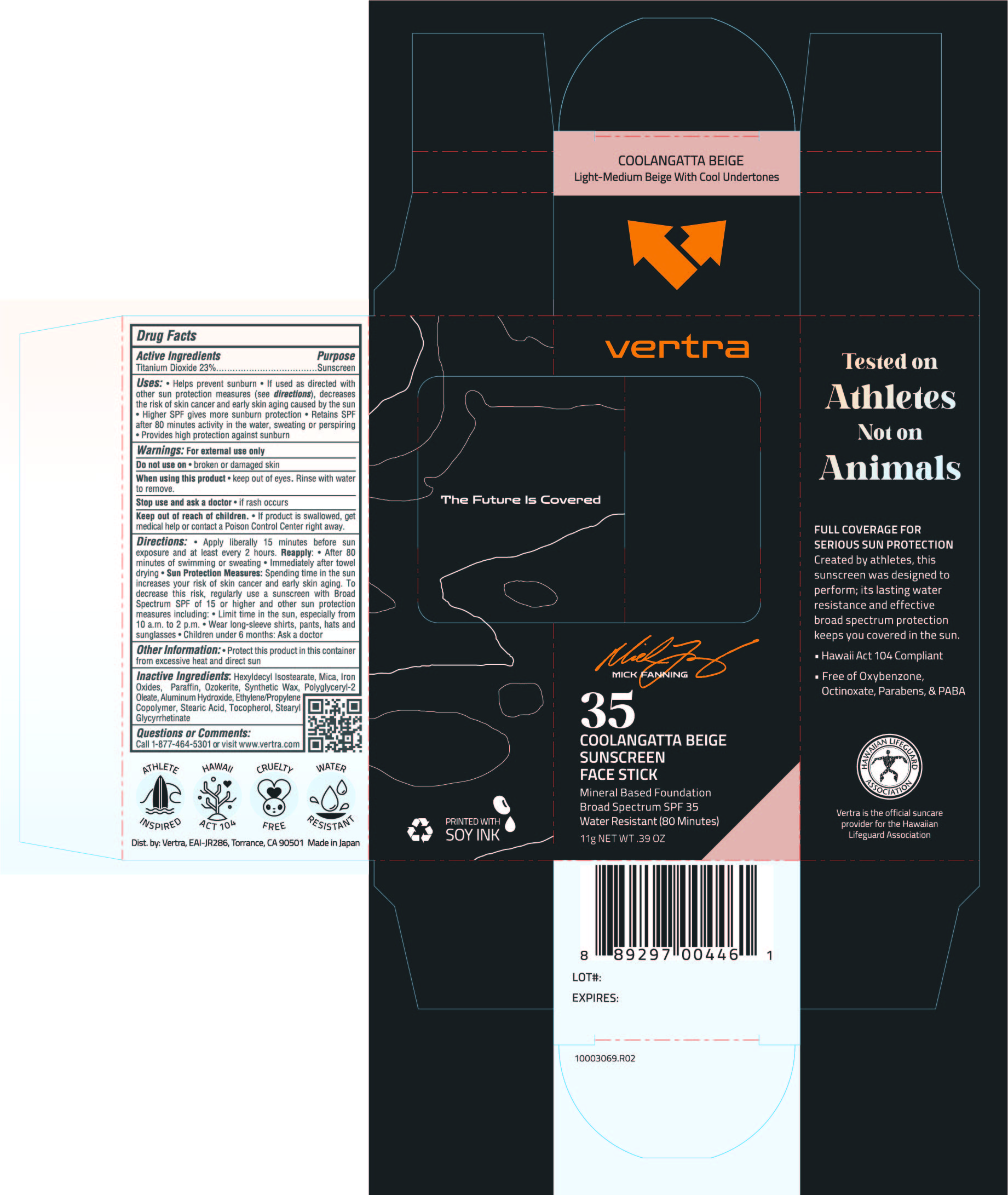 DRUG LABEL: Vertra Mick Fanning Signature Foundation Sunscreen Face Stick SPF 35 Coolangatta Beige
NDC: 71014-090 | Form: STICK
Manufacturer: EAI-JR 286, Inc.
Category: otc | Type: HUMAN OTC DRUG LABEL
Date: 20251007

ACTIVE INGREDIENTS: TITANIUM DIOXIDE 23 g/100 g
INACTIVE INGREDIENTS: FERRIC OXIDE RED; POLYGLYCERYL-2 OLEATE; STEARYL GLYCYRRHETINATE; FERROSOFERRIC OXIDE; HEXYLDECYL ISOSTEARATE; MICA; STEARIC ACID; CERESIN; SYNTHETIC WAX (1200 MW); FERRIC OXIDE YELLOW; ALUMINUM HYDROXIDE; PARAFFIN; TOCOPHEROL

Vertra Mick Fanning Signature Foundation Sunscreen Face Stick SPF 35 Coolangatta Beige

ACTIVE INGREDIENT

Titanium Dioxide 23%..............Sunscreen

PURPOSE

- Helps prevent sunburn.
- If used as directed with other sun protection measures (see directions), decreases the risk of skin cancer and early skin aging caused by the sun.
- Higher SPF gives more sunburn protection.
- Retains SPF after 80 minutes activity in the water, sweating or perspiring.
- Provides high protection against sunburn.

KEEP OUT OF REACH OF CHILDREN

If product is swallowed, get medical help or contact a Poison Control Center right away.

Stop use and ask a doctor if:

- Rash or irritation develops and lasts.

Do not use:

- On damaged or broken skin

When using this product:

- Keep out of eyes. Rinse with water to remove.

For external use only.

DOSAGE AND ADMINISTRATION

- Apply liberally and generously 15 minutes before sun exposure and at least every 2 hours.
- Children under 6 months of age: ask a doctor.
- Sun Protection Measures Spending time in the sun increases your risk of skin cancer and early skin aging. To decrease this risk, regularly use a sunscreen with a Broad Spectrum SPF value of 15 or higher and other sun protection measures including:
- Limit your time in the sun, especially from 10 a.m. - 2 p.m.
- Wear long-sleeved shirts, pants, hats, and sunglasses
- Reapply:
- After 80 minutes of swimming or sweating
- Immediately after towel drying
- At least every 2 hours

INACTIVE INGREDIENT

Hexyldecyl Isostearate, Aluminum Hydroxide, Mica, Iron Oxides, Stearic Acid, Paraffin, Ozokerite, Synthetic Wax, Ethylene/Propylene Copolymer, Polyglyceryl-2 Oleate, Tocopherol, Stearyl Glycyrrhetinate, Fragrance

STORAGE AND HANDLING

Protect this product in this container from excessive heat and direct sun

PACKAGE LABEL

vertra

35

Coolangatta Beige Face Stick

Mineral Based Foundation

Broad Spectrum SPF35

Water Resistant (80 Minutes)

11g NET WT. 0.39 OZ